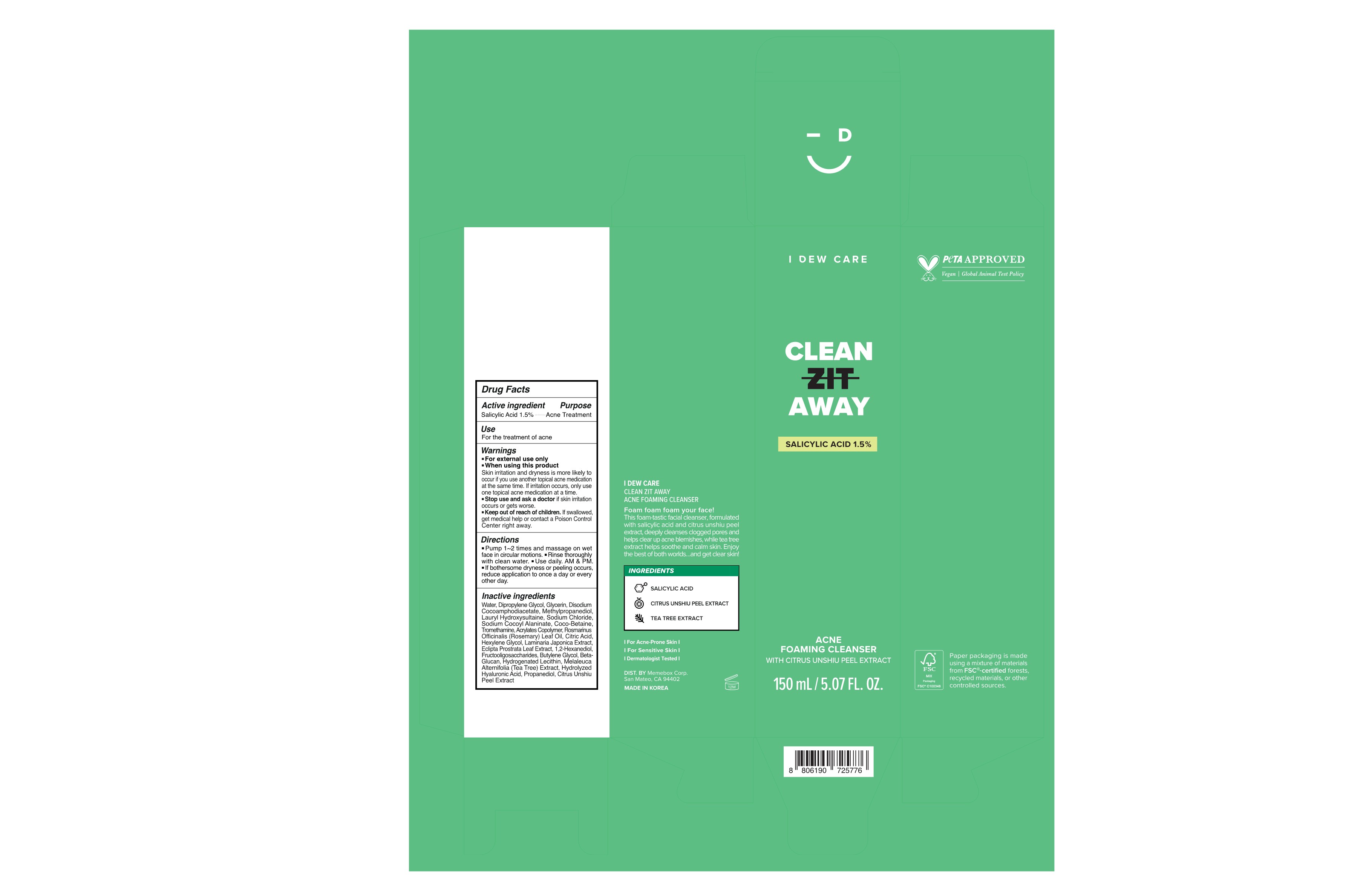 DRUG LABEL: I DEW CARE CLEAN ZIT AWAY ACNE FOAMING CLEANSER
NDC: 82904-414 | Form: LIQUID
Manufacturer: Memebox Corporation
Category: otc | Type: HUMAN OTC DRUG LABEL
Date: 20260101

ACTIVE INGREDIENTS: SALICYLIC ACID 1.5 g/100 mL
INACTIVE INGREDIENTS: BUTYLENE GLYCOL; HYDROGENATED SOYBEAN LECITHIN; GLYCERIN; DISODIUM COCOAMPHODIACETATE; TROMETHAMINE; ROSEMARY OIL; HEXYLENE GLYCOL; ECLIPTA PROSTRATA LEAF; TANGERINE PEEL; WATER; METHYLPROPANEDIOL; SODIUM CHLORIDE; BETA VULGARIS ROOT FRUCTOOLIGOSACCHARIDES; LAURYL HYDROXYSULTAINE; COCO-BETAINE; 1,2-HEXANEDIOL; PROPANEDIOL; DIPROPYLENE GLYCOL; CITRIC ACID MONOHYDRATE; LAMINARIA JAPONICA

82904-414-50 MKT END 7-24-2027 I DEW CARE CLEAN ZIT AWAY ACNE FOAMING CLEANSER WITH CITRUS UNSHIU PEEL EXTRACT

Active Ingredient

Salicylic acid 1.5%

Purpose

Acne Treatment

Use

For the treatment of acne

Warnings

■ For external use only

■ When using this product Skin irritation and dryness is more likely to occur if you use another topical acne medication at the same time. If irritation occurs, only use one topical acne medication at a time.

■ Stop use and ask a doctor if skin irritation occurs or gets worse.

■ Keep out of reach of children. If swallowed, get medical help or contact a Poison Control Center right away.

Directions

■ Pump 1~2 times and massage on wet face in circular motions. ■ Rinse thoroughly with clean water. ■ Use daily. AM & PM. ■ If bothersome dryness or peeling occurs, reduce application to once a day or every other day.

Inactive Ingredients

Water, Dipropylene Glycol, Glycerin, Disodium Cocoamphodiacetate, Methylpropanediol, Lauryl Hydroxysultaine, Sodium Chloride, Sodium Cocoyl Alaninate, Coco-Betaine, Tromethamine, Acrylates Copolymer, Rosmarinus Officinalis (Rosemary) Leaf Oil, Citric Acid, Hexylene Glycol, Laminaria Japonica Extract, Eclipta Prostrata Leaf Extract, 1,2-Hexanediol, Fructooligosaccharides, Butylene Glycol, Beta- Glucan, Hydrogenated Lecithin, Melaleuca Alternifolia (Tea Tree) Extract, Hydrolyzed Hyaluronic Acid, Propanediol, Citrus Unshiu Peel Extract

OTHER SAFETY INFORMATION

For Acne-Prone Skin
For Sensitive Skin
Non-Comedogenic
Dermatologist Tested

DIST. BY
Memebox Corp.
San Mateo, CA 94402

MADE IN KOREA